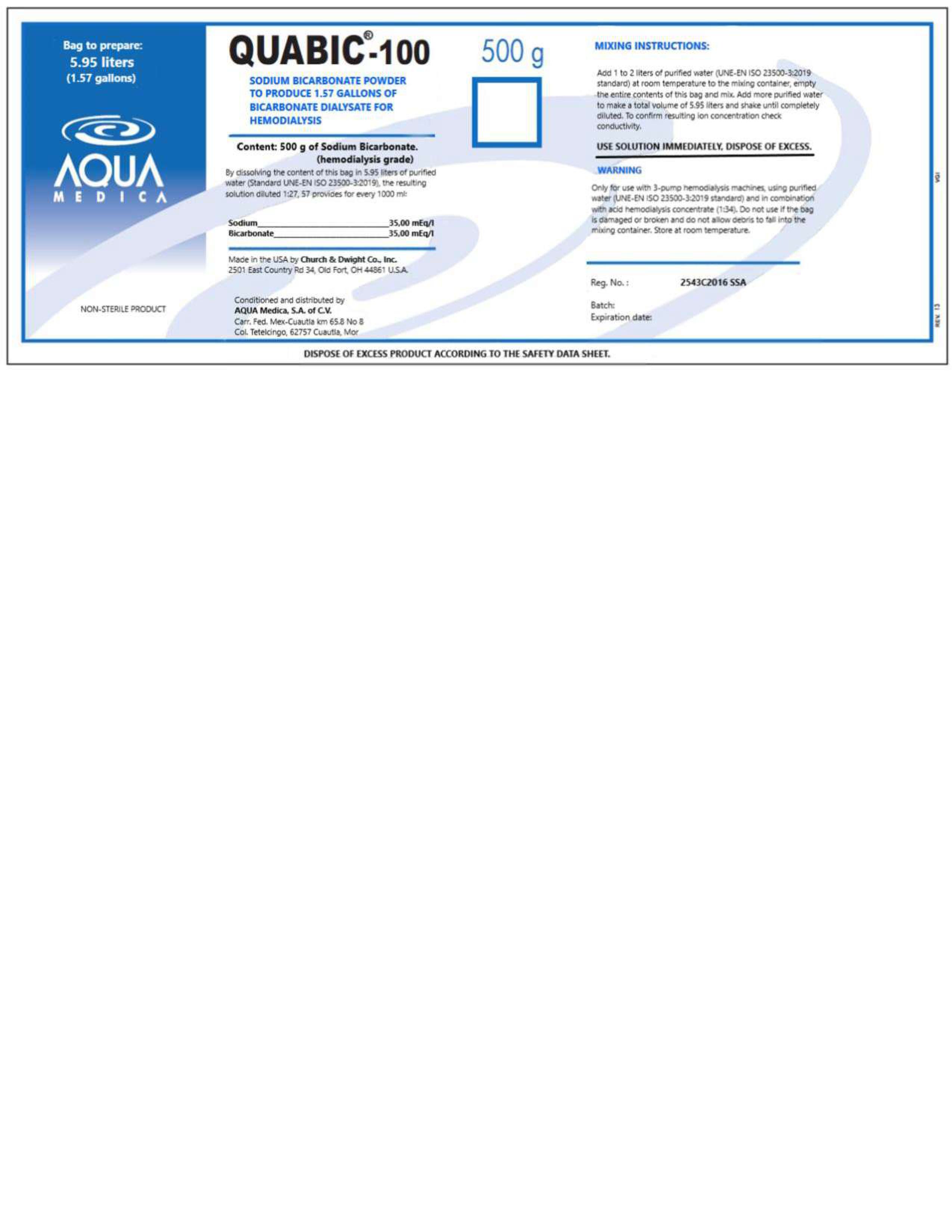 DRUG LABEL: QUABIC-100
NDC: 81943-503 | Form: SOLUTION, CONCENTRATE
Manufacturer: Aqua Medica, S.A. de C.V.
Category: otc | Type: HUMAN OTC DRUG LABEL
Date: 20251110

ACTIVE INGREDIENTS: SODIUM BICARBONATE 8.4 g/100 mL
INACTIVE INGREDIENTS: WATER

This is a Hemodialyhsis-Grade Sodium Bicarbonate Solution.

This solution already diluted 1.27:57 with purified water (standard 13959:2014), provides:

Sodium: 35.0 mEq/L

Each 1000 mL of this solution conteins:

Sodium bicarbonate USP, hemodialysis grade: 84.0 g

Purified water (standard iso 13959:2014), csp: 1000 mL

ACTIVE INGREDIENT

Sodium Bicarbonate: Antiseptic

PURPOSE

For use only with 3-pump hemodialysis machines.

INDICATIONS AND USAGE

Use only with 3-pump hemodialysis machines, together with acid concentrate for hemodialysis, diluting with purified water (standar ISO 13959:2014) IN A RATIO 1:1

WARNINGS

This solution should be transparent and colorless. Do not use if cloudy or with broken seal. If not all of the contents are used, discard the excess. Keep at room temperature.

DOSAGE AND ADMINISTRATION

For use only with 3-pump hemodialysis machines, together with acid concentrate for hemodialysis, diluting with purified water.

DO NOT USE

If cloudy or with borken seal.

WHEN USING

If not all the contents are used, discard the excess.

Keep out of reach of children. If swallowed, get medical help or contact a Poison Control Center right away.

STORAGE AND HANDLING

Keep at room temperature.

INACTIVE INGREDIENT

Purified water (standard ISO 13959:2014)

PACKAGE LABEL

81943-503-03